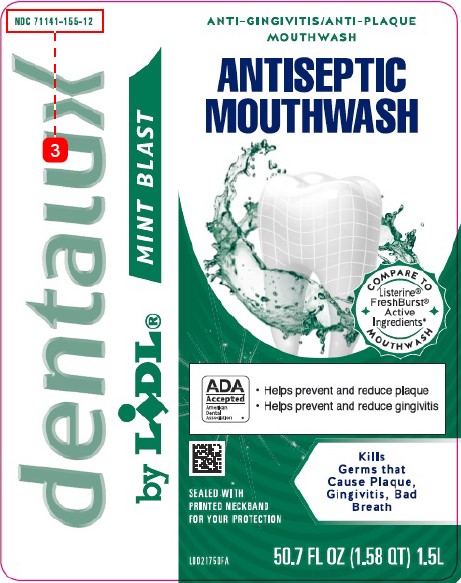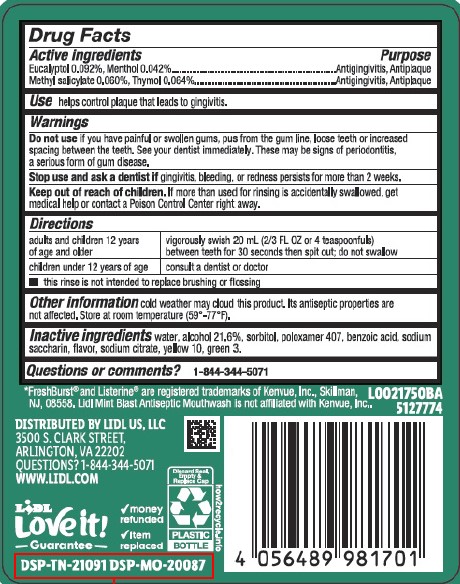 DRUG LABEL: Antiseptic Mouthrinse
NDC: 71141-155 | Form: MOUTHWASH
Manufacturer: Lidl US, LLC
Category: otc | Type: HUMAN OTC DRUG LABEL
Date: 20260204

ACTIVE INGREDIENTS: EUCALYPTOL 0.92 mg/1 mL; MENTHOL 0.42 mg/1 mL; METHYL SALICYLATE 0.6 mg/1 mL; THYMOL 0.64 mg/1 mL
INACTIVE INGREDIENTS: ALCOHOL; SORBITOL; POLOXAMER 407; BENZOIC ACID; SACCHARIN SODIUM; SODIUM CITRATE; D&C YELLOW NO. 10; FD&C GREEN NO. 3; WATER

Dentalux 072.003/072AL rev 2-072AN
Spring Mint Antiseptic Mouthrinse

Active ingredients

Eucalyptol 0.092%

Menthol 0.042%

Methyl sailcylate 0.060%

Thymol 0.064%

PURPOSE

Antigingivitis, Antiplaque

Use

Helps control plaque that leads to gingivitis

Warnings

For this product

Do not use

if you have painful or swollen gums, pus from the gum line, loose teeth or increased spacing between the teeth. See your dentist immediately. These may be signs of periodontitis, a serious form of gum disease.

Stop use and ask a dentist if

gingivitis, bleeding, or redness persists for more than 2 weeks.

Keep out of reach of children.

If more than used for rinsing is accidentally swallowed, get medical help or contact a Poison Control Center right away.

Directions

adults and children under 12 years if age and older - vigorously swish 20 ml (2/3 FL OZ or 4 teaspoonfuls) between teeth for 30 seconds then spit out; do not swallow

children under 12 years of age - consult a dentist or doctor

- this rinse is not intended to replace brushng or flossing

Other information

cold weather may cloud this product. Its antiseptic properties are not affected. Store at room temperature (59° -77° F).

Inactive ingredients

water, alcohol 21.6 %, sorbitol, poloxamer 407, benzoic acid, sodium saccharin, flavor, sodium citrate, yellow 10, green 3

Questions or comments?

1-844-344-5071

Disclaimer

*Freshburst®and Listerine®are registered trademarks of Kenvue, Inc., Skillman, NJ, 08558. Lidl Mint Blast Antiseptic Mouthwash is not affiliated with Kenvue, Inc.

Adverse Reactions Section

DISTRIBUTED BY Lidl US, LLC

3500 S. Clark Street

Arlington, VA 22202

QUESTIONS? 1-844-344-5071

WWW.LIDL.COM

Lidl Love it! Guarantee

- money refunded
- Item replaced

DSP-TN-21091 DSP-MO-20087

PRINCIPAL DISPLAY PANEL

NDC 71141-155-12

dentalux by Lidl®

MINT BLAST

ANTI-GINGIVITIS/ANTI-PLAQUE MOUTHWASH

ANTISEPTIC MOUTHWASH

COMPARE TO Listerine® FreshBurst©Active Ingredients* MOUTHWASH

ADA Accepted

American Dental Association

- Helps prevent and reduce plaque
- Helps prevent and reduce gingivitis

Kills Germs that Cause Plaque, Gingivitis, Bad Breath

SEALED WITH PRINTED NECKBAND FOR YOUR PROTECTION

50.7 FL OZ (1.58 QT) 1.5L